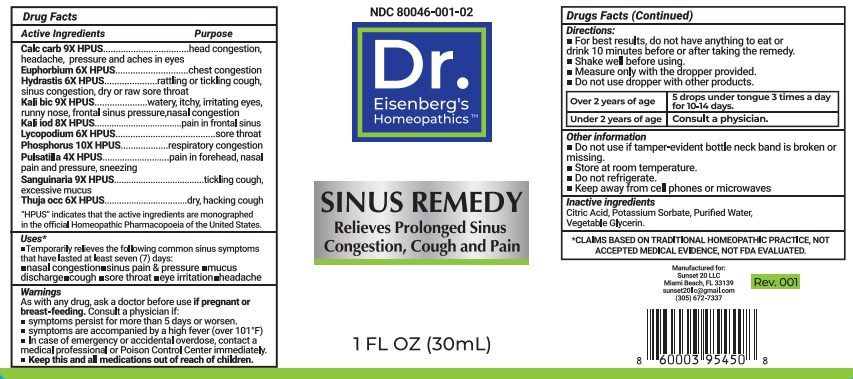 DRUG LABEL: Sinus Remedy
NDC: 80046-001 | Form: LIQUID
Manufacturer: Sunset 20 LLC
Category: homeopathic | Type: HUMAN OTC DRUG LABEL
Date: 20210309

ACTIVE INGREDIENTS: OYSTER SHELL CALCIUM CARBONATE, CRUDE 9 [hp_X]/30 mL; EUPHORBIA RESINIFERA RESIN 6 [hp_X]/30 mL; GOLDENSEAL 6 [hp_X]/30 mL; POTASSIUM DICHROMATE 9 [hp_X]/30 mL; POTASSIUM IODIDE 8 [hp_X]/30 mL; LYCOPODIUM CLAVATUM SPORE 6 [hp_X]/30 mL; PHOSPHORUS 10 [hp_X]/30 mL; PULSATILLA VULGARIS WHOLE 4 [hp_X]/30 mL; SANGUINARIA CANADENSIS ROOT 9 [hp_X]/30 mL; THUJA OCCIDENTALIS LEAFY TWIG 6 [hp_X]/30 mL
INACTIVE INGREDIENTS: CITRIC ACID ACETATE; POTASSIUM SORBATE; WATER; GLYCERIN

SINUS REMEDY

Active Ingredients / Purpose

Calc carb 9X HPUS .......... head congestion, headache, pressure and aches in eyes

Euphorbium 6X HPUS .......... chest congestion

Hydrastis 6X HPUS .......... rattling or tickling cough, sinus congestion, dry or raw sore throat

Kali bic 9X HPUS .......... watery, itchy, irritating eyes, runny nose, frontal sinus pressue, nasal congestion

Kali iod 8X HPUS .......... pain in frontal sinus

Lycopodium 6X HPUS .......... sore throat

Phosphorus 10X HPUS .......... respiratory congestion

Pulsatilla 4X HPUS .......... pain in forehead, nasal pain, and pressure, sneezing

Sanguinaria 9X HPUS .......... tickling cough, excessive muscus

Thuja occ 6X HPUS .......... dry, hacking cough

"HPUS" indicates that the active ingredients are monographed in the official Homeopathic Pharmacopoeia of the United States.

*CLAIMS BASED ON TRADITIONAL HOMEOPATHIC PRACTICE, NOT ACCEPTED MEDICAL EVIDENCE, NOT FDA EVALUATED.

Uses*

- Temporarily relieves the following common sinus symptoms that have lasted at least seven (7) days:
- nasal congestion •sinus pain & pressure •mucus discharge •cough •sore throat •eye irritation •headache

Warnings

As with any drug, ask a doctor before use if pregnant or breast-feeding. Consult a physician if:

- symptoms persist for more than 5 days or worsen.
- symptoms are accompanied by a high fever (over 101° F)
- In case of emergency or accidental overdose, contact a medical professional or Poison Control Center Immediately.

KEEP OUT OF REACH OF CHILDREN

- Keep this and all medications out of reach of children.

Directions:

- For best results, do not have anything to eat or drink 10 minutes before or after taking the remedy.
- Shake well before using.
- Measure only with the dropper provided.
- Do not use dropper with other products.

Over 2 years of age | 5 drops under tongue 3 times a day for 10-14 days.
Under 2 years of age | Consult a physician.

Other information

- Do not use if tamper-evident bottle neck band is broken or missing.
- Store at room temperature.
- Do not refrigerate.
- Keep away from cell phones or microwaves

Inactive ingredients

Citric Acid, Potassium Sorbate, Purified Water, Vegetable Glycerin.

QUESTIONS

Manufactured for:

Sunset 20 LLC

Miami Beach, FL 33139

sunset20llc@gmail.com

(305) 672-7337

PACKAGE LABEL

PURPOSE

NDC: 80046-001-02

Dr.

Eisenberg's

Homeopathics™

SINUS REMEDY

Relieves Prolonged Sinus

Congestion, Cough and Pain

1 FL OZ (30mL)

Rev.001